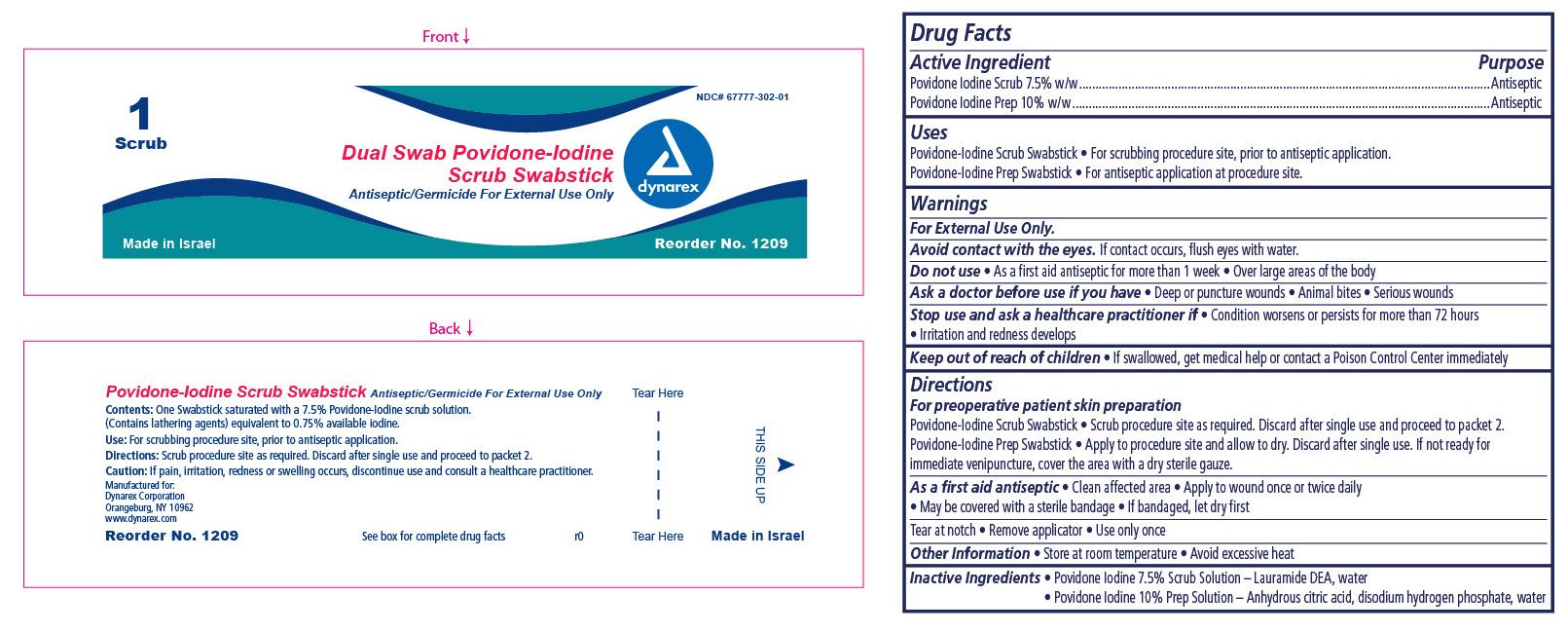 DRUG LABEL: Dual Swab Scrub Swabstick
NDC: 67777-302 | Form: SWAB
Manufacturer: Dynarex Corporation
Category: otc | Type: HUMAN OTC DRUG LABEL
Date: 20151103

ACTIVE INGREDIENTS: POVIDONE-IODINE 7.5 g/100 g
INACTIVE INGREDIENTS: LAURIC DIETHANOLAMIDE; WATER

Dual Swab Povidone Iodine Scrub Swabstick

Active Ingredient

Active ingredient Purpose

Povidone iodine 7.5% Antiseptic

Purpose

For scrubbing procedure site, prior to antiseptic application

Indications and usage

For pre-operative patient skin preparation.

Warnings

For External Use Only

Avoid contact with the eyes. If contact occurs, flush with water.

Stop use

Stop use and ask a healthcare professional if,

- condition worsens or persists for more than 72 hours
- if pain, irritation, redness or swelling occurs

Ask a doctor before use if you have

- deep puncture wounds
- animal bites
- serious wounds

Do not use

- as a first aid antiseptic for more than 1 week
- over large areas of the body

Keep out of reach of children

- if swallowed, get medical help or contact a Poison Control Center immediately.

Dosage and administration

Directions

For preoperative patient skin preparation:

- scrub procedure site as required. Discard after single use and proceed to packet 2.

As a first aid antiseptic:

- clean affected area
- apply to wound once or twice daily
- may be covered with a sterile bandage
- if bandaged, let dry first.

Tear at notch, remove applicator, use only once.

Inactive ingredients

Lauramide DEA, Water

Other information

- Store at room temperature
- Avoid excessive heat

Principal Display Panel

Dynarex Dual Swab Povidone Iodine Scrub Swabstick

Item #: 1209

1209 Scrub.jpg